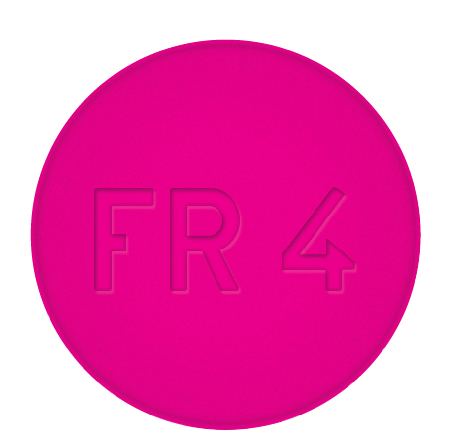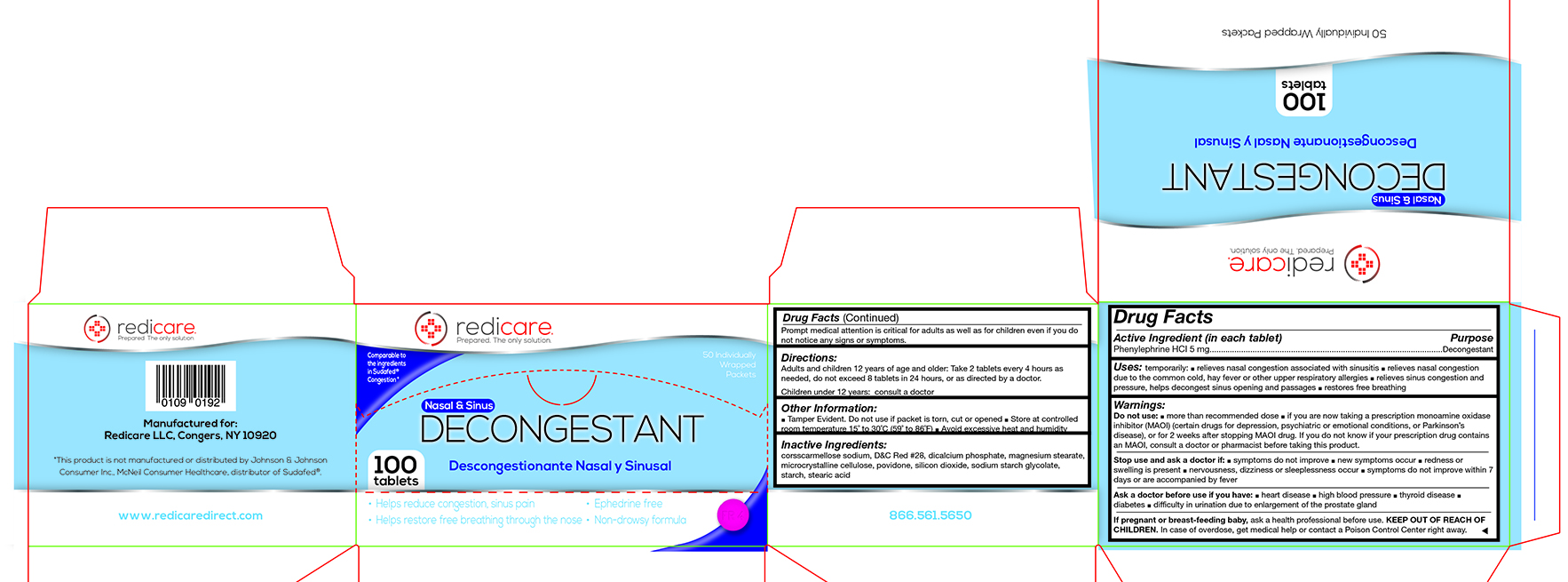 DRUG LABEL: Nasal and Sinus Decongestant
NDC: 71105-333 | Form: TABLET
Manufacturer: Redicare LLC
Category: otc | Type: HUMAN OTC DRUG LABEL
Date: 20210702

ACTIVE INGREDIENTS: PHENYLEPHRINE HYDROCHLORIDE 5 mg/1 1
INACTIVE INGREDIENTS: CROSCARMELLOSE SODIUM; D&C RED NO. 28; CALCIUM PHOSPHATE, DIBASIC, DIHYDRATE; MAGNESIUM STEARATE; CELLULOSE, MICROCRYSTALLINE; POVIDONE; SILICON DIOXIDE; SODIUM STARCH GLYCOLATE TYPE A CORN; STARCH, CORN; STEARIC ACID

Decongestant

Active Ingredient (in each tablet)........................................................ Purpose

Phenylephrine HCI 5 mg.......................................................................................................Decongestant

Uses:

Temporarily: ■ relieves nasal congestion associated with sinusitis ■ relieves nasal congestion due to the common cold, hay fever or other upper respiratory allergies ■ relieves sinus congestion and pressure, helps decongest sinus opening and passages ■ restores free breathing

Warnings:

Do not use:

■ more than recommended dose ■ if you are now taking a prescription monoamine oxidase inhibitor (MAOI) (certain drugs for depression, psychiatric or emotional conditions, or Parkinson’s disease), or for 2 weeks after stopping MAOI drug. If you do not know if your prescription drug contains a MAOI, consult a doctor or pharmacist before taking this product.

Stop use and ask a doctor if

■ symptoms do not improve ■ new symptoms occur ■ redness or swelling is present ■ nervousness, dizziness or sleeplessness occur ■ symptoms do not improve within 7 days or are accompanied by fever

Ask a doctor before use if you have:

■ heart disease ■ high blood pressure ■ thyroid disease ■ diabetes ■ difficulty in urination due to enlargement of the prostate gland

If pregnant or breast-feeding a baby,

ask a health professional before use.

KEEP OUT OF REACH OF CHILDREN.

In a case of overdose, get medical help or contact a Poison Control Center right away. Prompt medical attention is critical for adults as well as for children even if you do not notice any signs or symptoms.

Directions:

Adults and children 12 years of age and older: Take 2 tablets every 4 hours as needed, do not exceed 8 tablets in 24 hours, or as directed by a doctor.
Children under 12 years: consult a doctor

Other Information:

■ Tamper Evident. Do not use if packet is torn, cut or opened ■ Store at controlled room temperature 15˚ to 30˚C (59˚ to 86˚F) ■ Avoid excessive heat and humidity

Inactive Ingredients:

corsscarmellose sodium, D&C Red #28, dicalcium phosphate, magnesium stearate, microcrystalline cellulose, povidone, silicon dioxide, sodium starch glycolate, starch, stearic acid